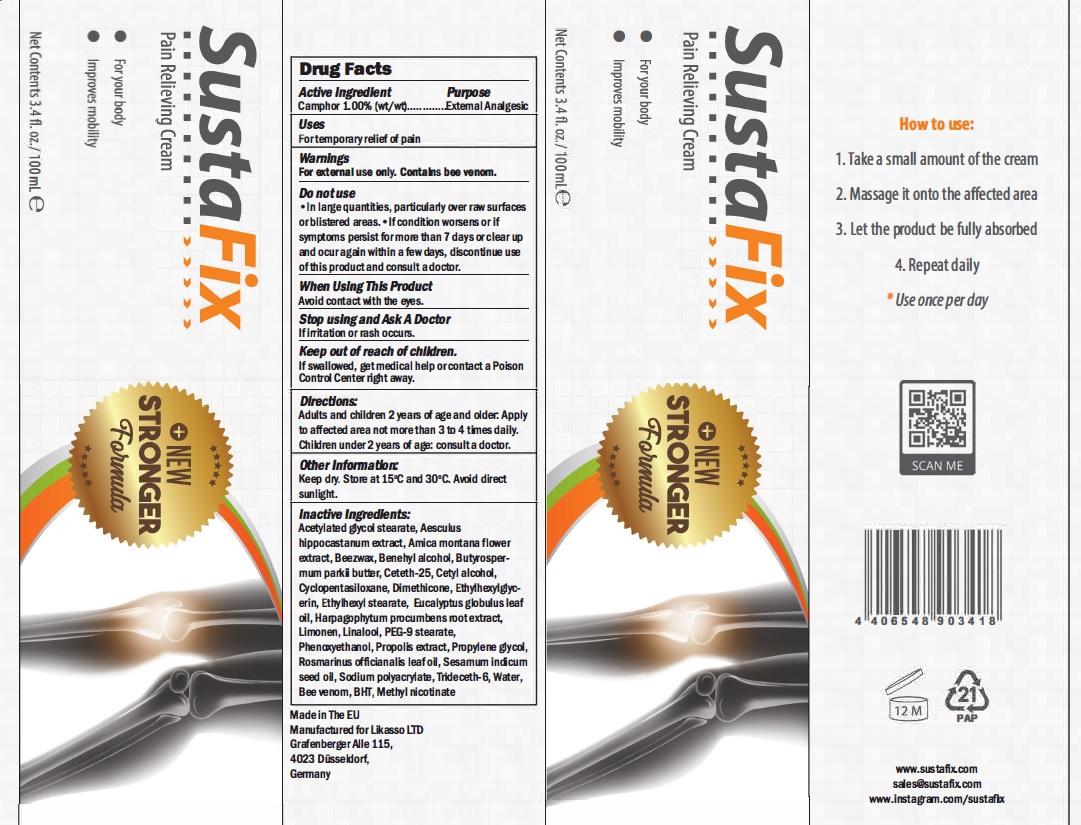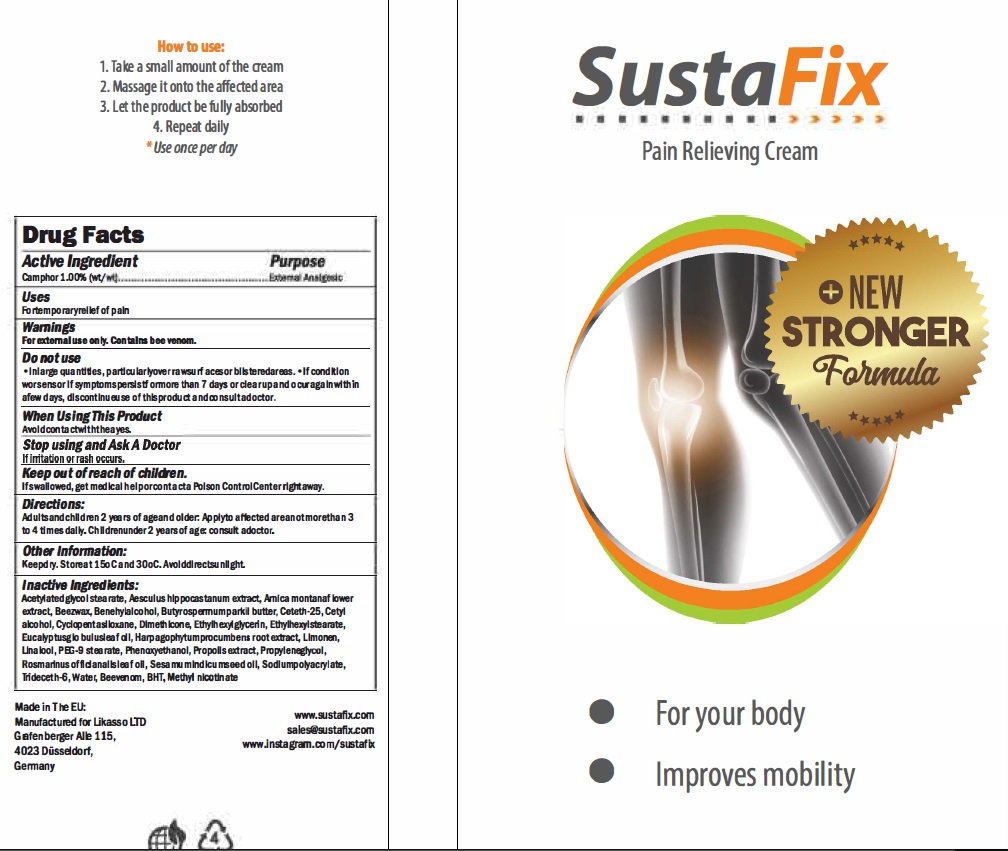 DRUG LABEL: SustaFix
NDC: 82225-002 | Form: CREAM
Manufacturer: Hakimian Global LLC
Category: otc | Type: HUMAN OTC DRUG LABEL
Date: 20211027

ACTIVE INGREDIENTS: CAMPHOR (NATURAL) 1 g/100 g
INACTIVE INGREDIENTS: AESCULUS HIPPOCASTANUM FLOWER; CETETH-25; CYCLOMETHICONE 5; EUCALYPTUS GLOBULUS LEAF; PHENOXYETHANOL; ROSMARINUS OFFICINALIS FLOWER; ARNICA MONTANA FLOWER; BENZYL ALCOHOL; LINALOOL, (+)-; SODIUM BENZOATE; WATER; LIMONENE, (+)-; SYNTHETIC BEESWAX; PROPYLENE GLYCOL; BUTYROSPERMUM PARKII (SHEA) BUTTER UNSAPONIFIABLES; SODIUM POLYACRYLATE (8000 MW); APIS MELLIFERA VENOM; GLYCOL STEARATE; CETYL ALCOHOL; DIMETHICONE; ETHYLHEXYLGLYCERIN; ETHYLHEXYL STEARATE; BUTYLATED HYDROXYTOLUENE; METHYL NICOTINATE; PEG-9 STEARATE; HARPAGOPHYTUM PROCUMBENS ROOT; PROPOLIS WAX; SESAMUM INDICUM WHOLE; TRIDECETH-6

Sustafix (Hakimian Global LLC | 82225-002-10)

Active Ingredient

Camphor 1.00%

Purpose

External Analgesic

Uses

For temporary relief of pain

Warnings

For external use only. Contains bee venom.

Do Not use

In large quantities, particularly over raw surfaces or blistered areas.• If condition worsens or if symptoms persist for more than 7 days or clear up and ocur again within a few days, discontinue use of this product and consult a doctor.

When Using This Product

Avoid contact with the eyes

Stop using and Ask a Doctor

if irritation or rash occurs.

Keep Out Of Reach of Children

If swallowed, get medical help or contact a Poison Control Center right away.

Directions

Adults and children 2 years of age and older: Apply to affected area not more than 3 to 4 times daily. Children under 2 years of age: consult a doctor.

Other Information

Keep dry. Store at 15°C and 30°C. Avoid direct sunlight.

Inactive Ingredients

Acetylated glycol stearate, Aesculus hippocastanum extract, Amica montana flower extract, Beezwax, Benehyl alcohol, Butyrospermum parkii butter, Ceteth-251 Cet:yl alcohol, Cyclopentasiloxane, Dimethicone, Ethylhexylglycerin, Ethylhexyl stearate, EucalypbJs globulus leaf oil, Harpagophytum procumbens root extract, Limonen, Linalool, PEG-9 stearate, Phenoxyethanol, Propolis extract, Propylene glycol, Rosmarinus officianalis leaf oil, Sesamum indicum seed oil, Sodium polyacrylate, Trideceth-61 Water, Bee venom, BHT1 Methyl nicotinate

Principal Display

Made in the EU

Manufacturered for Likasso, LTD

Grafenberger Alle 115

4023 Dusseldorf, Germany

NDC: 82225-002-10